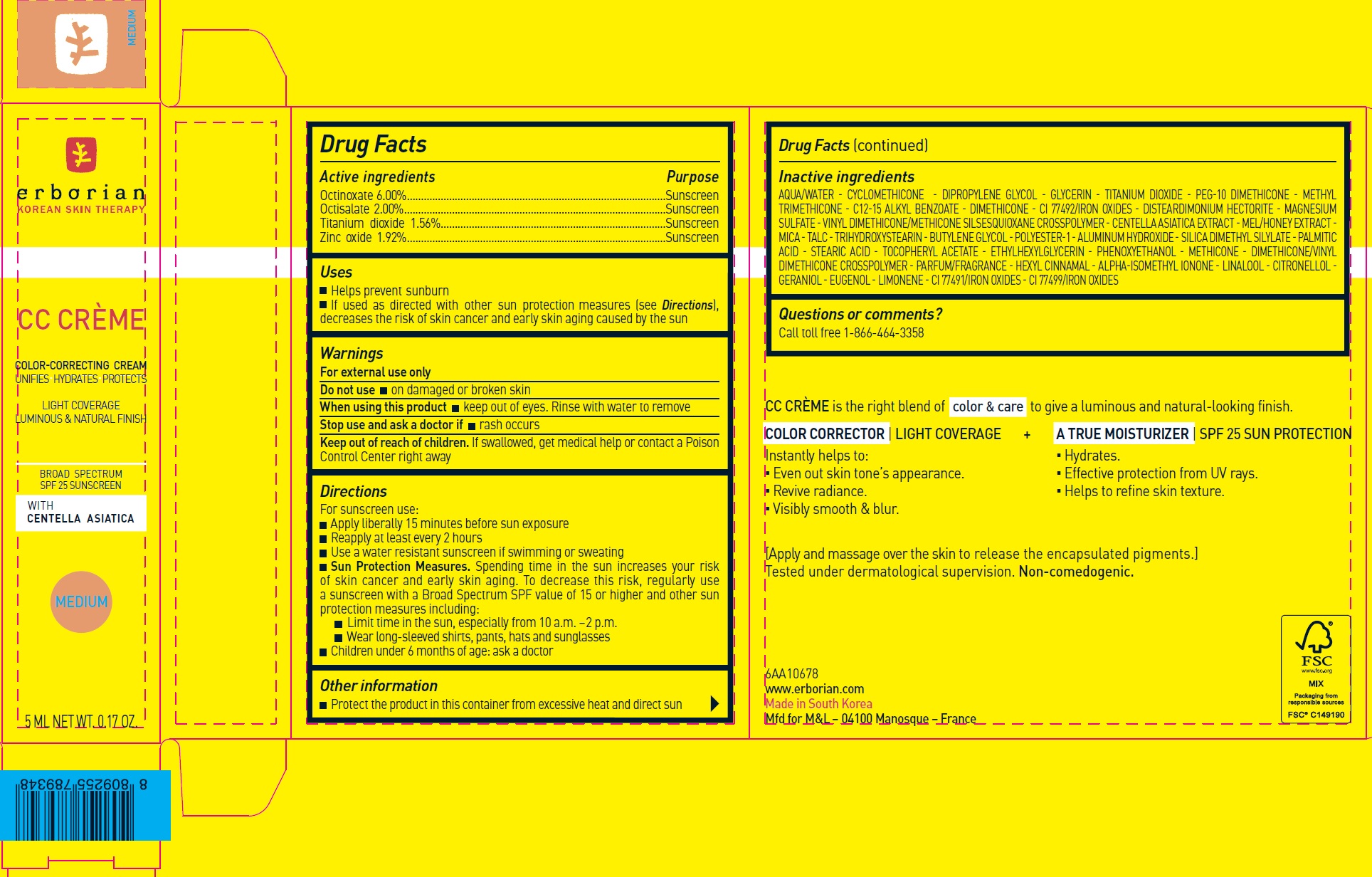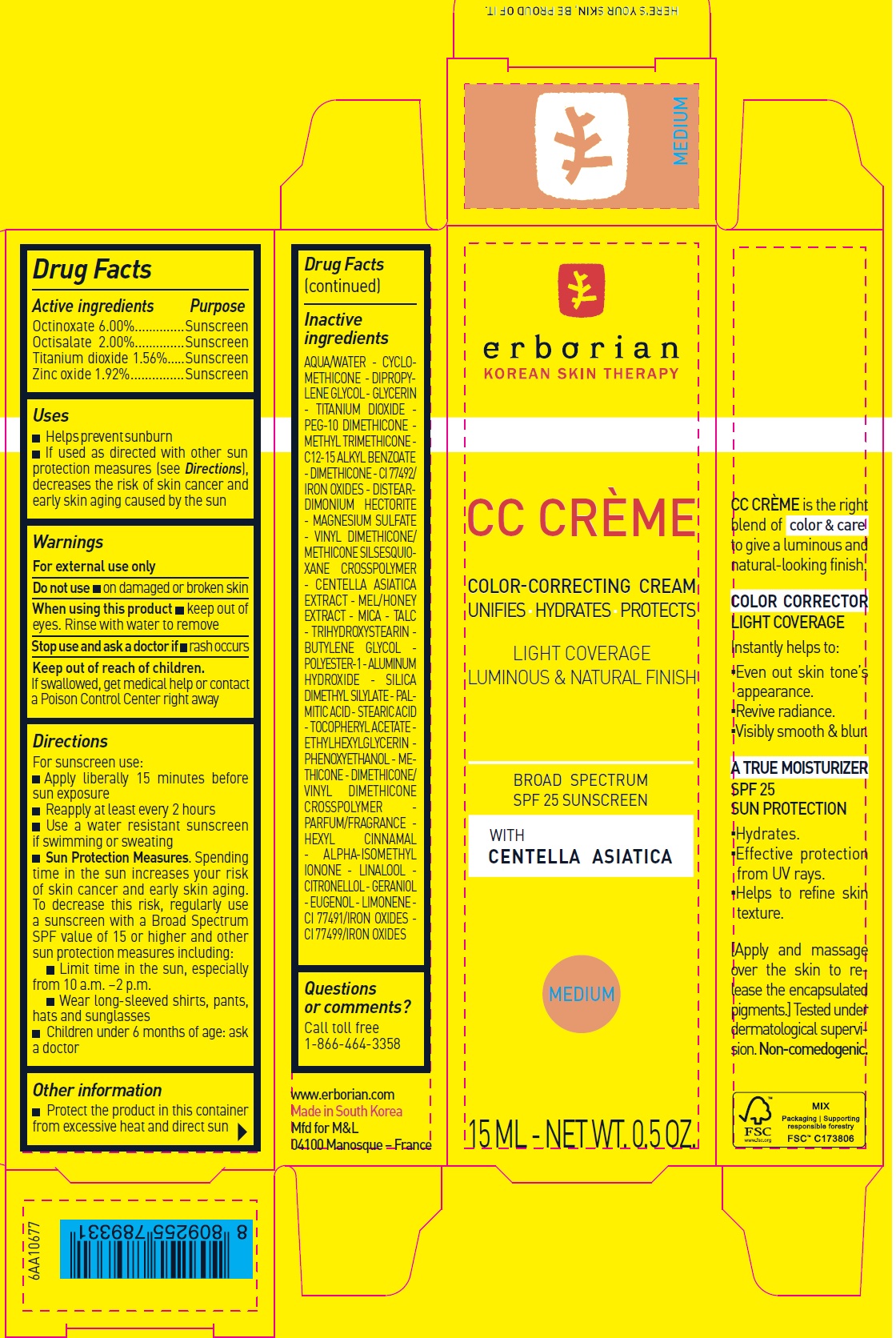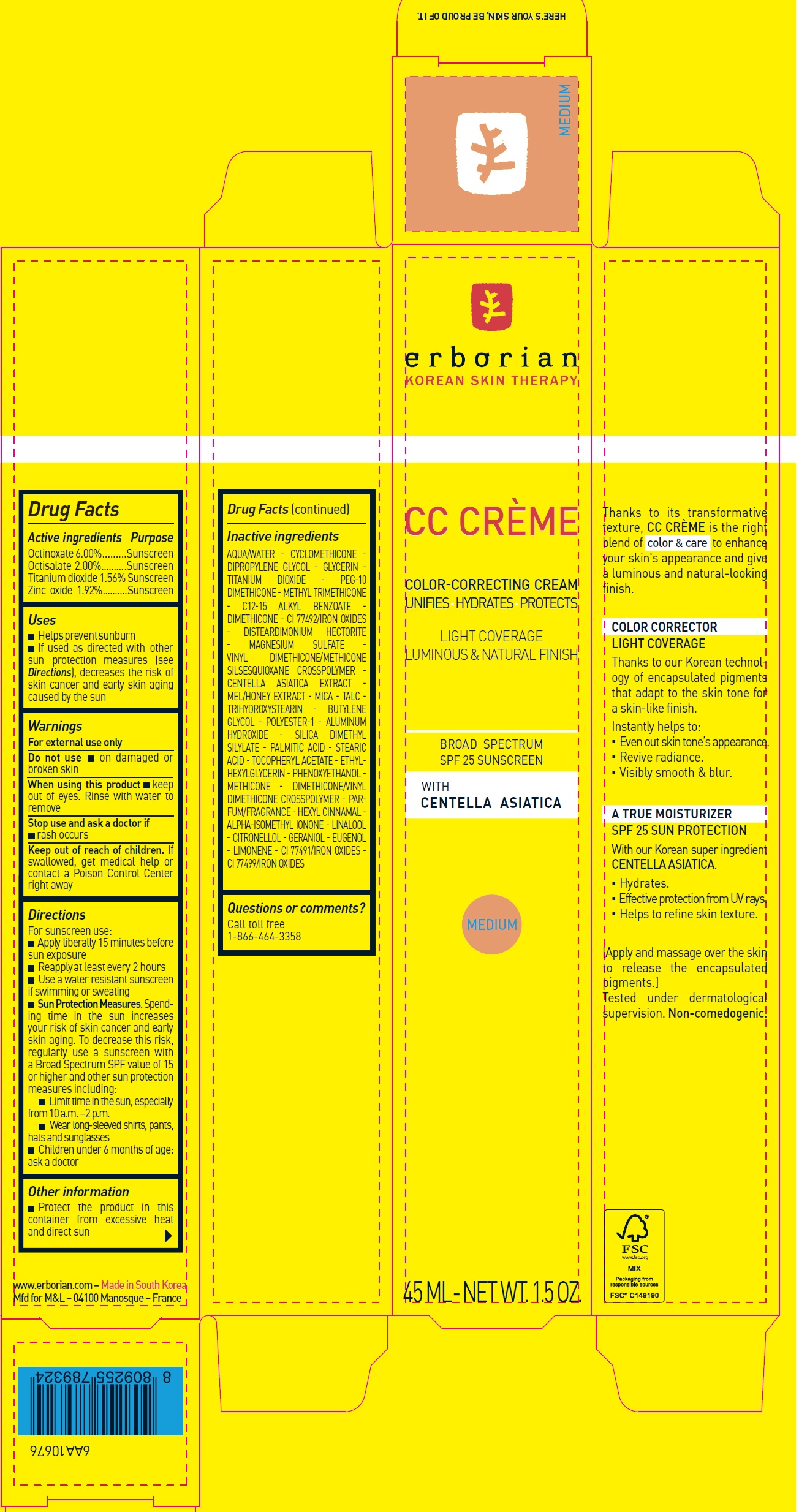 DRUG LABEL: ERBORIAN CC CREME Color Correcting SPF 25 MEDIUM
NDC: 10345-951 | Form: CREAM
Manufacturer: LABORATOIRES M&L
Category: otc | Type: HUMAN OTC DRUG LABEL
Date: 20250812

ACTIVE INGREDIENTS: OCTINOXATE 60 mg/1 mL; OCTISALATE 20 mg/1 mL; TITANIUM DIOXIDE 15.6 mg/1 mL; ZINC OXIDE 19.2 mg/1 mL
INACTIVE INGREDIENTS: WATER; CYCLOMETHICONE; DIPROPYLENE GLYCOL; GLYCERIN; METHYL TRIMETHICONE; C12-15 ALKYL BENZOATE; DIMETHICONE; FERRIC OXIDE YELLOW; DISTEARDIMONIUM HECTORITE; MAGNESIUM SULFATE; VINYL DIMETHICONE/METHICONE SILSESQUIOXANE CROSSPOLYMER; CENTELLA ASIATICA TRITERPENOIDS; MICA; TALC; TRIHYDROXYSTEARIN; BUTYLENE GLYCOL; ALUMINUM HYDROXIDE; SILICA DIMETHYL SILYLATE; PALMITIC ACID; STEARIC ACID; .ALPHA.-TOCOPHEROL ACETATE; ETHYLHEXYLGLYCERIN; PHENOXYETHANOL; .ALPHA.-HEXYLCINNAMALDEHYDE; ISOMETHYL-.ALPHA.-IONONE; LINALOOL, (+/-)-; CITRONELLOL; GERANIOL; EUGENOL; LIMONENE, (+)-; FERRIC OXIDE RED; FERROSOFERRIC OXIDE

ERBORIAN CC CREME Color Correcting Cream SPF 25, MEDIUM

Active ingredients

Octinoxate 6.00%
Octisalate 2.00%
Titanium dioxide 1.56%
Zinc oxide 1.92%

Purpose

Sunscreen

Uses

- Helps prevent sunburn
- If used as directed with other sun protection measures (see Directions), decreases the risk of skin cancer and early skin aging caused by the sun

Warnings

For external use only

Do not use

- on damaged or broken skin

When using this product

- keep out of eyes. Rinse with water to remove

Stop use and ask a doctor if

- rash occurs

Keep out of reach of children.

If swallowed, get medical help or contact a Poison Control Center right away

Directions

For sunscreen use:

- Apply liberally 15 minutes before sun exposure
- Reapply at least every 2 hours
- Use a water resistant sunscreen if swimming or sweating
- Sun Protection Measures.Spending time in the sun increases your risk of skin cancer and early skin aging. To decrease this risk, regularly use a sunscreen with a Broad Spectrum SPF value of 15 or higher and other sun protection measures including:
- Limit time in the sun, especially from 10 a.m. –2 p.m.
- Wear long-sleeved shirts, pants, hats and sunglasses
- Children under 6 months of age: ask a doctor

Other information

- Protect the product in this container from excessive heat and direct sun

Inactive ingredients

AQUA/WATER - CYCLOMETHICONE - DIPROPYLENE GLYCOL - GLYCERIN - TITANIUM DIOXIDE - PEG-10 DIMETHICONE - METHYL TRIMETHICONE - C12-15 ALKYL BENZOATE - DIMETHICONE - CI 77492/IRON OXIDES - DISTEARDIMONIUM HECTORITE - MAGNESIUM SULFATE - VINYL DIMETHICONE/METHICONE SILSESQUIOXANE CROSSPOLYMER - CENTELLA ASIATICA EXTRACT - MEL/HONEY EXTRACT - MICA - TALC -TRIHYDROXYSTEARIN - BUTYLENE GLYCOL - POLYESTER-1 - ALUMINUM HYDROXIDE - SILICA DIMETHYL SILYLATE - PALMITIC ACID - STEARIC ACID - TOCOPHERYL ACETATE - ETHYLHEXYLGLYCERIN - PHENOXYETHANOL - METHICONE - DIMETHICONE/VINYL DIMETHICONE CROSSPOLYMER - PARFUM/FRAGRANCE - HEXYL CINNAMAL - ALPHA-ISOMETHYL IONONE - LINALOOL - CITRONELLOL - GERANIOL - EUGENOL - LIMONENE - CI 77491/IRON OXIDES - CI 77499/IRON OXIDES

Questions or comments?

Call toll free 1-866-464-3358